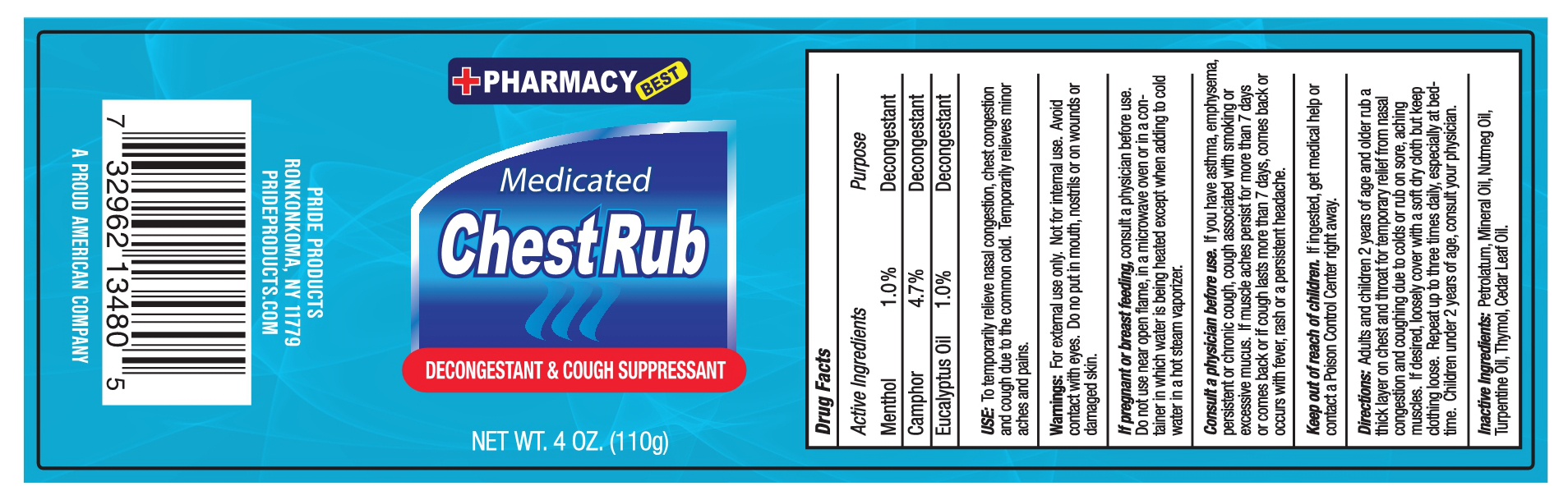 DRUG LABEL: 4OZ MEDICATED CHEST RUB
NDC: 81984-099 | Form: OINTMENT
Manufacturer: Pride Products Corporation
Category: otc | Type: HUMAN OTC DRUG LABEL
Date: 20171220

ACTIVE INGREDIENTS: MENTHOL 1 g/100 g; EUCALYPTUS OIL 1 g/100 g; CAMPHOR (SYNTHETIC) 4.7 g/100 g
INACTIVE INGREDIENTS: PETROLATUM; MINERAL OIL; NUTMEG OIL; TURPENTINE OIL; THYMOL; CEDAR LEAF OIL

ACTIVE INGREDIENTS

Active Ingredients Purpose

Menthol 1.0% Decongestant

camphor 4.7% Decongestant

Eucalyptus Oil 1.0 % Decongestant

Purpose

Decongestant

USE:

To temporarily relieve nasal congestion, chest congestion and cough due to the common cold. Temporarily relieves minor aches and pains.

Warnings:

For external use only. Not for internal use. Avoil contact with eyes. Do not put in mouth, nostrils or on wounds or damaged skin.

If pregnant or breast feeding,

consult a physician before use.

Do not use near open flame, in a microwave oven or in a container in which water is being heated except when adding to cold water in a hot steam vaporizer.

Consult a physician before use.

If you have asthma, emphysema, persistent or chronic cough, cough associated with smoking or excessive mucus. If muscle aches persist for more than 7 days or comes back or if cough lasts more than 7 days, come back or occurs with fever, rash or a persistent headache.

Keep out of reach of children.

If ingested, get medical help or contact a Posion Control Center right away.

Directions:

Adults and children 2 years of age and older rub a thick layer on chest and throat for temporary relief from nasal congestion and coughing due to colds or rub on sore, aching muscles. If desired, loosely cover with a soft dry cloth but keep clothing loose. Repeat up to three times daily, especially at bedtime. children under 2 years of age, consult your physician.

Inactive Ingredients:

Petrolatum, Mineral Oil, Nutmeg Oil, Turpentine Oil, Thymol, Cedar Leaf Oil.